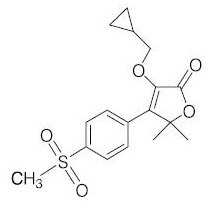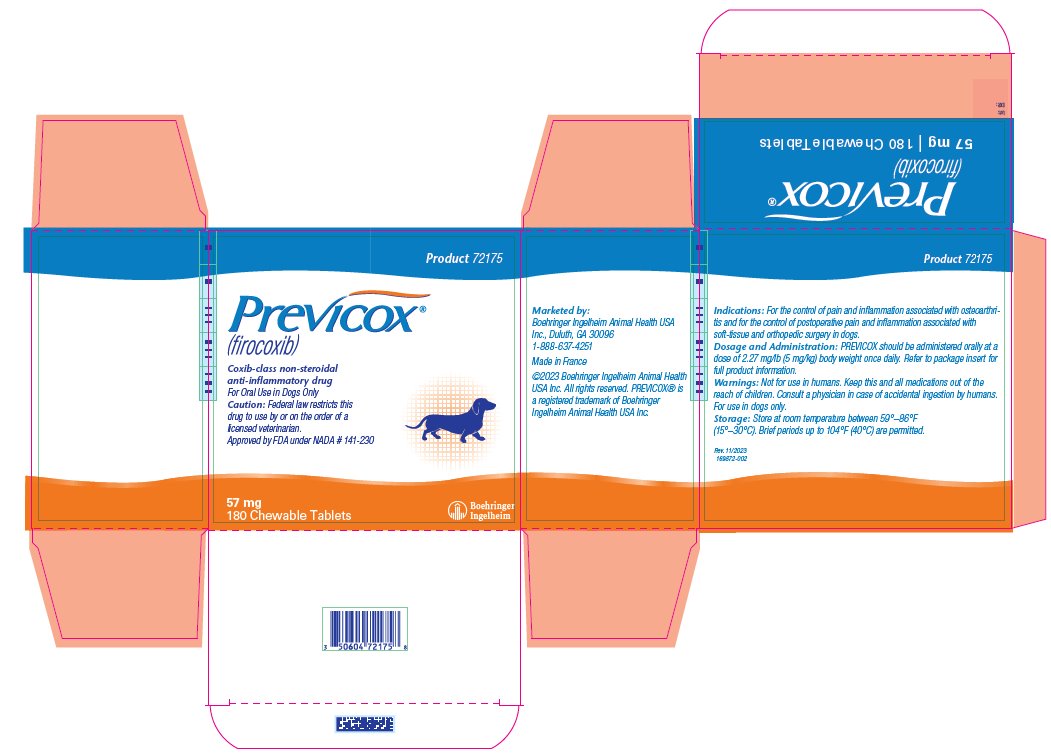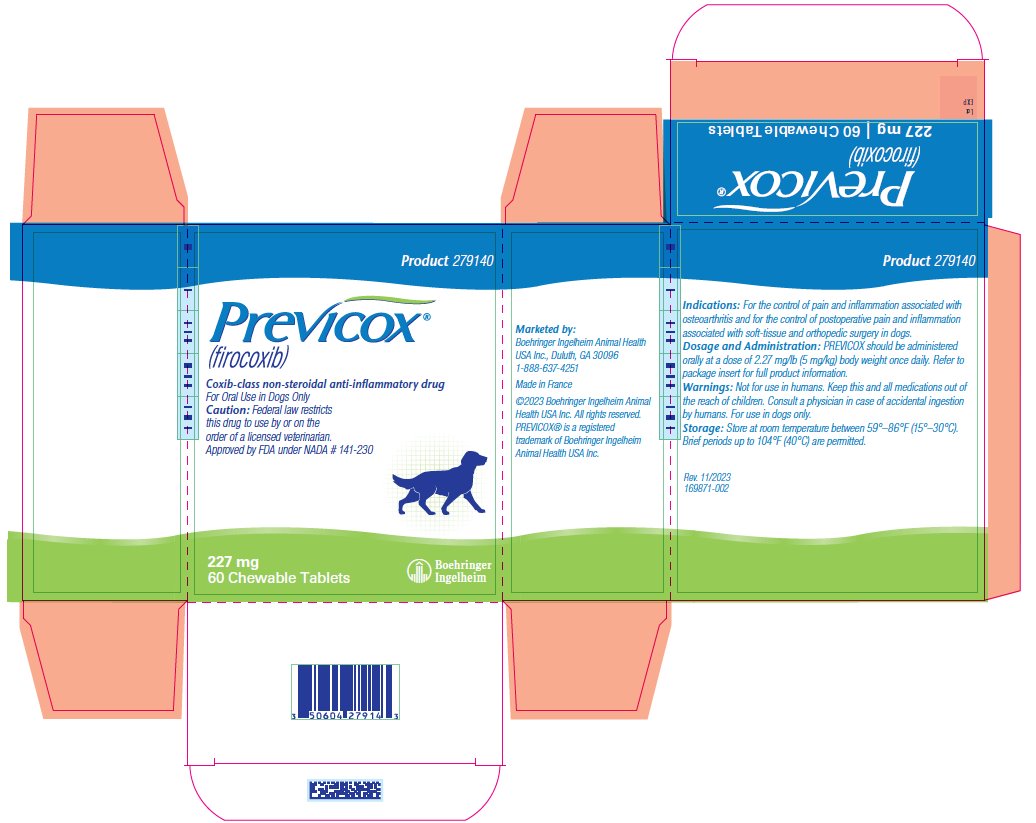 DRUG LABEL: PREVICOX
NDC: 0010-9150 | Form: TABLET, CHEWABLE
Manufacturer: Boehringer Ingelheim Animal Health USA Inc
Category: animal | Type: PRESCRIPTION ANIMAL DRUG LABEL
Date: 20241213

ACTIVE INGREDIENTS: FIROCOXIB 57 mg/1 1

PREVICOX® (firocoxib)
Chewable Tablets

For oral use in dogs only.

Caution: Federal law restricts this drug to use by or on the order of a licensed veterinarian.

DESCRIPTION

Description: PREVICOX (firocoxib) belongs to the coxib class of non-narcotic, non-steroidal anti-inflammatory drugs. Firocoxib is a white crystalline compound described chemically as 3-(cyclopropylmethoxy)-4-(4-(methylsulfonyl)phenyl)- 5,5-dimethylfuranone. The empirical formula is C17H20O5S, and the molecular weight is 336.4. The structural formula is shown below:

PHARMACOKINETICS

Pharmacokinetics: The absolute bioavailability of PREVICOX (firocoxib) is approximately 38% when administered as a 5 mg/kg oral dose to fasted adult dogs. Firocoxib is rapidly cleared from the blood via hepatic metabolism and fecal excretion (CLsystemic = ~0.4 L/hr/kg). Despite a high level of plasma protein binding (96%), firocoxib exhibits a large volume of distribution (Vdλ of total drug = ~4.6 L/kg) and a terminal elimination half life of 7.8 hours (%CV = 30%). The oral drug absorption process is highly variable among subjects. Co-administration of PREVICOX with food delays drug absorption (Tmax from 1 to 5 hours) and decreases peak concentrations (Cmax from 1.3 to 0.9 mcg/mL). However, food does not affect the overall oral bioavailability at the recommended dose.

INDICATIONS AND USAGE

Indications: PREVICOX (firocoxib) Chewable Tablets are indicated for the control of pain and inflammation associated with osteoarthritis and for the control of postoperative pain and inflammation associated with soft-tissue and orthopedic surgery in dogs.

Dosage and Administration: Always provide the Client Information Sheet with prescription. Carefully consider the potential benefits and risks of PREVICOX and other treatment options before deciding to use PREVICOX. Use the lowest effective dose for the shortest duration consistent with individual response. The recommended dosage of PREVICOX (firocoxib) for oral administration in dogs is 2.27 mg/lb (5.0 mg/kg) body weight once daily as needed for osteoarthritis and for 3 days as needed for postoperative pain and inflammation associated with soft-tissue and orthopedic surgery. The dogs can be treated with PREVICOX approximately two hours prior to surgery. The tablets are scored and dosage should be calculated in half tablet increments. PREVICOX Chewable Tablets can be administered with or without food.

CONTRAINDICATIONS

Contraindications: Dogs with known hypersensitivity to firocoxib should not receive PREVICOX.

WARNINGS

Warnings: Not for use in humans. Keep this and all medications out of the reach of children. Consult a physician in case of accidental ingestion by humans.

For oral use in dogs only. Use of this product at doses above the recommended 2.27 mg/lb (5.0 mg/kg) in puppies less than seven months of age has been associated with serious adverse reactions, including death (see Animal Safety). Due to tablet sizes and scoring, dogs weighing less than 12.5 lb (5.7 kg) cannot be accurately dosed.

All dogs should undergo a thorough history and physical examination before the initiation of NSAID therapy. Appropriate laboratory testing to establish hematological and serum baseline data is recommended prior to and periodically during administration of any NSAID.

Owners should be advised to observe for signs of potential drug toxicity (see Adverse Reactions and Animal Safety) and be given a Client Information Sheet about PREVICOX Chewable Tablets.

For technical assistance or to report suspected adverse events, call 1-888-637-4251.

For additional information about adverse drug experience reporting for animal drugs, contact FDA at 1-888-FDA-VETS or www.fda.gov/reportanimalae.

PRECAUTIONS

Precautions: This product cannot be accurately dosed in dogs less than 12.5 pounds in body weight.

Consider appropriate washout times when switching from one NSAID to another or when switching from corticosteroid use to NSAID use.

As a class, cyclooxygenase inhibitory NSAIDs may be associated with renal, gastrointestinal and hepatic toxicity. Sensitivity to drug-associated adverse events varies with the individual patient. Dogs that have experienced adverse reactions from one NSAID may experience adverse reactions from another NSAID. Patients at greatest risk for adverse events are those that are dehydrated, on concomitant diuretic therapy, or those with existing renal, cardiovascular, and/or hepatic dysfunction. Concurrent administration of potentially nephrotoxic drugs should be carefully approached and monitored. NSAIDs may inhibit the prostaglandins that maintain normal homeostatic function. Such anti-prostaglandin effects may result in clinically significant disease in patients with underlying or pre-existing disease that has not been previously diagnosed. Since NSAIDS possess the potential to produce gastrointestinal ulceration and/or gastrointestinal perforation, concomitant use of Previcox Chewable Tablets with other anti-inflammatory drugs, such as NSAIDs or corticosteroids, should be avoided. The concomitant use of protein bound drugs with PREVICOX Chewable Tablets has not been studied in dogs. Commonly used protein-bound drugs include cardiac, anticonvulsant, and behavioral medications. The influence of concomitant drugs that may inhibit the metabolism of PREVICOX Chewable Tablets has not been evaluated. Drug compatibility should be monitored in patients requiring adjunctive therapy.

If additional pain medication is needed after the daily dose of PREVICOX, a non-NSAID class of analgesic may be necessary.

Appropriate monitoring procedures should be employed during all surgical procedures. Anesthetic drugs may affect renal perfusion, approach concomitant use of anesthetics and NSAIDs cautiously. The use of parenteral fluids during surgery should be considered to decrease potential renal complications when using NSAIDs perioperatively.

The safe use of PREVICOX Chewable Tablets in pregnant, lactating or breeding dogs has not been evaluated.

Adverse Reactions:

Osteoarthritis: In controlled field studies, 128 dogs (ages 11 months to 15 years) were evaluated for safety when given PREVICOX Chewable Tablets at a dose of 2.27 mg/lb (5.0 mg/kg) orally once daily for 30 days. The following adverse reactions were observed. Dogs may have experienced more than one of the observed adverse reactions during the study.

Adverse Reactions Seen in U.S. Field Studies
Adverse Reactions | Previcox n=128 | Active Control n=121
Vomiting | 5 | 8
Diarrhea | 1 | 10
Decreased Appetite or Anorexia | 3 | 3
Lethargy | 1 | 3
Pain | 2 | 1
Somnolence | 1 | 1
Hyperactivity | 1 | 0

PREVICOX (firocoxib) Chewable Tablets were safely used during field studies concomitantly with other therapies, including vaccines, anthelmintics, and antibiotics.

Soft-tissue Surgery: In controlled field studies evaluating soft-tissue postoperative pain and inflammation, 258 dogs (ages 10.5 weeks to 16 years) were evaluated for safety when given PREVICOX Chewable Tablets at a dose of 2.27 mg/lb (5.0 mg/kg) orally approximately 2 hours prior to surgery and once daily thereafter for up to two days. The following adverse reactions were observed. Dogs may have experienced more than one of the observed reactions during the study.

Adverse Reactions Seen in the Soft-tissure Surgery Postoperative Pain Field Studies
Adverse Reactions | Firocoxib Group n=127 | Control Group [Sham-dosed (pilled)] n=131
Vomiting | 5 | 6
Diarrhea | 1 | 1
Bruising at Surgery Site | 1 | 1
Respiratory Arrest | 1 | 0
SQ Crepitus in Rear Leg and Flank | 1 | 0
Swollen Paw | 1 | 0

Orthopedic Surgery: In a controlled field study evaluating orthopedic postoperative pain and inflammation, 226 dogs of various breeds, ranging in age from 1 to 11.9 years in the PREVICOX-treated groups and 0.7 to 17 years in the control group were evaluated for safety. Of the 226 dogs, 118 were given PREVICOX Chewable Tablets at a dose of 2.27 mg/lb (5.0 mg/kg) orally approximately 2 hours prior to surgery and once daily thereafter for a total of three days. The following adverse reactions were observed. Dogs may have experienced more than one of the observed reactions during the study.

Adverse Reactions Seen in the Orthopedic Surgery Postoperative Pain Field Study
Adverse Reactions | Firocoxib Group n=118 | Control Group [Sham-dosed (pilled).] n=108
Vomiting | 1 | 0
Diarrhea | 2 [One dog had hemorrhagic gastroenteritis.] | 1
Bruising at Surgery Site | 2 | 3
Inappetence/Decreased Appetite | 1 | 2
Pyrexia | 0 | 1
Incision Swelling, Redness | 9 | 5
Oozing Incision | 2 | 0
A case may be represented in more than one category.

Post-Approval Experience (Rev. 2009): The following adverse reactions are based on post-approval adverse drug event reporting. The categories are listed in decreasing order of frequency by body system:

Gastrointestinal: vomiting, anorexia, diarrhea, melena, gastrointestinal perforation, hematemesis, hematachezia, weight loss, gastrointestinal ulceration, peritonitis, abdominal pain, hypersalivation, nausea

Urinary: elevated BUN, elevated creatinine, polydypsia, polyuria, hematuria, urinary incontinence, proteinuria, kidney failure, azotemia, urinary tract infection

Neurological/Behavioral/Special Sense: depression/lethargy, ataxia, seizures, nervousness, confusion, weakness, hyperactivity, tremor, paresis, head tilt, nystagmus, mydriasis, aggression, uveitis.

Hepatic: elevated ALP, elevated ALT, elevated bilirubin, decreased albumin, elevated AST, icterus, decreased or increased total protein and globulin, pancreatitis, ascites, liver failure, decreased BUN

Hematological: anemia, neutrophilia, thrombocytopenia, neutropenia

Cardiovascular/Respiratory: tachypnea, dyspnea, tachycardia

Dermatologic/Immunologic: pruritis, fever, alopecia, moist dermatitis, autoimmune hemolytic anemia, facial/muzzle edema, urticaria

In some cases, death has been reported as an outcome of the adverse events listed above.

For technical assistance or to report suspected adverse events, call 1-888-637-4251. For additional information about adverse drug experience reporting for animal drugs, contact FDA at 1-888-FDA-VETS or www.fda.gov/reportanimalae.

INFORMATION FOR OWNERS/CAREGIVERS

Information For Dog Owners: PREVICOX, like other drugs of its class, is not free from adverse reactions. Owners should be advised of the potential for adverse reactions and be informed of the clinical signs associated with drug intolerance. Adverse reactions may include vomiting, diarrhea, decreased appetite, dark or tarry stools, increased water consumption, increased urination, pale gums due to anemia, yellowing of gums, skin or white of the eye due to jaundice, lethargy, incoordination, seizure, or behavioral changes. Serious adverse reactions associated with this drug class can occur without warning and in rare situations result in death (see Adverse Reactions). Owners should be advised to discontinue PREVICOX therapy and contact their veterinarian immediately if signs of intolerance are observed. The vast majority of patients with drug related adverse reactions have recovered when the signs are recognized, the drug is withdrawn, and veterinary care, if appropriate, is initiated. Owners should be advised of the importance of periodic follow up for all dogs during administration of any NSAID.

ANIMAL PHARMACOLOGY AND OR TOXICOLOGY

MECHANISM OF ACTION

Clinical Pharmacology: Mode of action: PREVICOX (firocoxib) is a cyclooxygenase-inhibiting (coxib) class, non-narcotic, non-steroidal anti-inflammatory drug (NSAID) with anti-inflammatory and analgesic properties. There are two main cyclooxygenase enzymes, COX-1 and COX-2, and a newly discovered third enzyme, COX-3, which has yet to be fully characterized.^1 Cyclooxygenase-1 (COX-1) is the enzyme responsible for facilitating constitutive physiologic processes, e.g., platelet aggregation, gastric mucosal protection, and renal perfusion.^2 It also is constitutively expressed in the brain, spinal cord, and reproductive tract.^3 Cyclooxygenase-2 (COX-2) is responsible for the synthesis of inflammatory mediators, but it is also constitutively expressed in the brain, spinal cord and kidneys.^(4, 5, 6) Cyclooxygenase-3 (COX-3) is also constitutively expressed in the canine and human brain and also the human heart.^7 Results from in vitro studies showed firocoxib to be highly selective for the COX-2 enzyme when canine blood was exposed to drug concentrations comparable to those observed following a once daily 5 mg/kg oral dose in dogs.^8 However, the clinical significance of these findings has not been established.

Effectiveness: Two hundred and forty-nine dogs of various breeds, ranging in age from 11 months to 20 years, and weighing 13 to 175 lbs, were randomly administered PREVICOX or an active control drug in two field studies. Dogs were assessed for lameness, pain on manipulation, range of motion, joint swelling, and overall improvement in a non-inferiority evaluation of PREVICOX compared with the active control. At the study's end, 87% of the owners rated PREVICOX-treated dogs as improved. Eighty-eight percent of dogs treated with PREVICOX were also judged improved by the veterinarians. Dogs treated with PREVICOX showed a level of improvement in veterinarian-assessed lameness, pain on palpation, range of motion, and owner-assessed improvement that was comparable to the active control. The level of improvement in PREVICOX-treated dogs in limb weight bearing on the force plate gait analysis assessment was comparable to the active control.

In a separate field study, two hundred fifty-eight client-owned dogs of various breeds, ranging in age from 10.5 weeks to 16 years and weighing from 7 to 168 lbs, were randomly administered PREVICOX or a control (sham-dosed-pilled) for the control of postoperative pain and inflammation associated with soft-tissue surgical procedures such as abdominal surgery (e.g. ovariohysterectomy, abdominal cryptorchidectomy, splenectomy, cystotomy) or major external surgeries (e.g. mastectomy, skin tumor removal ≥8 cm). The study demonstrated that PREVICOX-treated dogs had significantly lower need for rescue medication than the control (sham-dosed-pilled) in controlling postoperative pain and inflammation associated with soft-surgery.

A multi-center field study with 226 client-owned dogs of various breeds, and ranging in age from 1 to 11.9 years in the PREVICOX-treated groups and 0.7 to 17 years in the control group was conducted. Dogs were randomly assigned to either the PREVICOX or the control (sham-dosed-pilled) group for the control of postoperative pain and inflammation associated with orthopedic surgery. Surgery to repair a ruptured cruciate ligament included the following stabilization procedures: fabellar suture and/or imbrication, fibular head transposition, tibial plateau leveling osteotomy (TPLO), and 'over the top' technique. The study (n = 220 for effectiveness) demonstrated that PREVICOX-treated dogs had significantly lower need for rescue medication than the control (sham-dosed-pilled) in controlling postoperative pain and inflammation associated with orthopedic surgery.

Palatability: PREVICOX Chewable Tablets were rated both convenient to administer (97.2%) and palatable to the dog (68.5%) by owners in multi-center field studies involving client-owned dogs of various breeds and sizes.

Animal Safety: In a target animal safety study, firocoxib was administered orally to healthy adult Beagle dogs (eight dogs per group) at 5, 15, and 25 mg/kg (1, 3, and 5 times the recommended total daily dose) for 180 days. At the indicated dose of 5 mg/kg, there were no treatment related adverse events. Decreased appetite, vomiting, and diarrhea were seen in dogs in all dose groups, including unmedicated controls, although vomiting and diarrhea were seen more often in dogs in the 5X dose group. One dog in the 3X dose group was diagnosed with juvenile polyarteritis of unknown etiology after exhibiting recurrent episodes of vomiting and diarrhea, lethargy, pain, anorexia, ataxia, proprioceptive deficits, decreased albumin levels, decreased and then elevated platelet counts, increased bleeding times, and elevated liver enzymes. On histopathologic examination, a mild ileal ulcer was found in one 5X dog. This dog also had a decreased serum albumin which returned to normal by study completion. One control and three 5X dogs had focal areas of inflammation in the pylorus or small intestine. Vacuolization without inflammatory cell infiltrates was noted in the thalamic region of the brain in three control, one 3X, and three 5X dogs. Mean ALP was within the normal range for all groups but was greater in the 3X and 5X dose groups than in the control group. Transient decreases in serum albumin were seen in multiple animals in the 3X and 5X dose groups, and in one control animal.

In a separate safety study, firocoxib was administered orally to healthy juvenile (10-13 weeks of age) Beagle dogs at 5, 15, and 25 mg/kg (1, 3, and 5 times the recommended total daily dose) for 180 days. At the indicated (1X) dose of 5 mg/kg, on histopathologic examination, three out of six dogs had minimal periportal hepatic fatty change. On histopathologic examination, one control, one 1X, and two 5X dogs had diffuse slight hepatic fatty change. These animals showed no clinical signs and had no liver enzyme elevations. In the 3X dose group, one dog was euthanized because of poor clinical condition (Day 63). This dog also had a mildly decreased serum albumin. At study completion, out of five surviving and clinically normal 3X dogs, three had minimal periportal hepatic fatty change. Of twelve dogs in the 5X dose group, one died (Day 82) and three moribund dogs were euthanized (Days 38, 78, and 79) because of anorexia, poor weight gain, depression, and in one dog, vomiting. One of the euthanized dogs had ingested a rope toy. Two of these 5X dogs had mildly elevated liver enzymes. At necropsy all five of the dogs that died or were euthanized had moderate periportal or severe panzonal hepatic fatty change; two had duodenal ulceration; and two had pancreatic edema. Of two other clinically normal 5X dogs (out of four euthanized as comparators to the clinically affected dogs), one had slight and one had moderate periportal hepatic fatty change. Drug treatment was discontinued for four dogs in the 5X group. These dogs survived the remaining 14 weeks of the study. On average, the dogs in the 3X and 5X dose groups did not gain as much weight as control dogs. Rate of weight gain was measured (instead of weight loss) because these were young growing dogs. Thalamic vacuolation was seen in three of six dogs in the 3X dose group, five of twelve dogs in the 5X dose group, and to a lesser degree in two unmedicated controls. Diarrhea was seen in all dose groups, including unmedicated controls.

In a separate dose tolerance safety study involving a total of six dogs (two control dogs and four treated dogs), firocoxib was administered to four healthy adult Beagle dogs at 50 mg/kg (ten times the recommended daily dose) for twenty-two days. All dogs survived to the end of the study. Three of the four treated dogs developed small intestinal erosion or ulceration. Treated dogs that developed small intestinal erosion or ulceration had a higher incidence of vomiting, diarrhea, and decreased food consumption than control dogs. One of these dogs had severe duodenal ulceration, with hepatic fatty change and associated vomiting, diarrhea, anorexia, weight loss, ketonuria, and mild elevations in AST and ALT. All four treated dogs exhibited progressively decreasing serum albumin that, with the exception of one dog that developed hypoalbuminemia, remained within normal range. Mild weight loss also occurred in the treated group. One of the two control dogs and three of the four treated dogs exhibited transient increases in ALP that remained within normal range.

STORAGE AND HANDLING

Storage: Store at room temperature, between 59°–86° F (15°–30° C). Brief periods up to 104° F (40° C) are permitted.

To Request a Safety Data Sheet (SDS), call 1-888-637-4251.

HOW SUPPLIED

How Supplied: PREVICOX is available as round, beige to tan, half-scored tablets in two strengths, containing 57 mg or 227 mg firocoxib. Each tablet strength is supplied in 3 count, 10 count and 30 count blister packages and 60 count and 180 count bottles.

REFERENCES

1. Willoughby DA, Moore AR and Colville-Nash PR. COX-1, COX-2, and COX-3 and the future treatment of chronic inflammatory disease. Lancet 2000;355:646-648.
2. Smith, et al., Pharmacological Analysis of Cyclo-oxygenase-1 in Inflammation. Proc. Natl. Acad. Sci. USA, Pharmacology 1998;95:13313-13318.
3. Jones CJ and Budsberg SC. Physiologic characteristics and clinical importance of the cyclooxygenase isoforms in dogs and cats. JAVMA 2000;217(5):721-729.
4. Zhang, et al., Inhibition of Cyclo-oxygenase-2 Rapidly Reverses Inflammatory Hyperalgesia and Prostaglandin E2 Production. JPET 1997;283:1069-1075.
5. Jones and Budsberg, pp. 721-729.
6. Zhang, et al., pp. 1069-1075.
7. Chandrasekharan NV, Dai H, et al. COX-3, a cyclooxygenase-1 variant inhibited by acetaminophen and other analgesic/antipyretic drugs: Cloning, structure and expression. Proc. Natl. Acad. Sci. USA, 2002;99(21):13926-13931.
8. Data on file.

Made in France
Marketed by: Boehringer Ingelheim Animal Health USA Inc., Duluth, GA 30096.
1-888-637-4251
Approved by FDA under NADA # 141-230
©2019 Boehringer Ingelheim Animal Health USA Inc. All Rights Reserved.
®PREVICOX is a registered trademark of Boehringer Ingelheim Animal Health USA Inc.

Rev. 12-2018

BOEHRINGER INGELHEIM

Information for Dog Owners about PREVICOX® (firocoxib) Chewable Tablets

PREVICOX Chewable Tablets are used for the control of pain and inflammation due to osteoarthritis or associated with soft-tissue and orthopedic surgery in your dog.

This summary contains important information about PREVICOX. You should read this information before you start giving your dog PREVICOX tablets and review it each time your prescription is refilled. This sheet is provided only as a summary and does not take the place of instructions from your veterinarian. Talk to your veterinarian if you do not understand any of this information or you want to know more about PREVICOX.

What is PREVICOX?

PREVICOX is a veterinary prescription non-steroidal anti-inflammatory drug (NSAID) used to control pain and inflammation due to osteoarthritis, or associated with soft-tissue and orthopedic surgery in dogs.

Osteoarthritis is a painful condition caused by "wear and tear" of cartilage and other parts of the joints that may result in the following changes or signs in your dog:

- Limping or lameness.
- Decreased activity or exercise (reluctance to stand, climb stairs, jump or run, or difficulty in performing these activities).
- Stiffness or decreased movement of joints.

PREVICOX is indicated for the control of postoperative pain and inflammation following soft-tissue and orthopedic surgeries (e.g. spays, cruciate ligament repair). Your veterinarian may administer PREVICOX before the procedure and recommend that the dog be treated for a few days after going home.

What kind of results can I expect when my dog is on PREVICOX for osteoarthritis?

While PREVICOX is not a cure for osteoarthritis, it can control the pain and inflammation and improve your dog's mobility.

- Response varies from dog to dog, but improvement can be quite dramatic.
- In most dogs, improvement can be seen within days.
- If PREVICOX is discontinued or not given as directed, your dog's pain and inflammation may return.

What kind of results can I expect when my dog is on PREVICOX for the control of pain and inflammation following soft-tissue and orthopedic surgery?

- PREVICOX Chewable Tablets allow your dog to recover more comfortably by controlling pain and inflammation following soft-tissue and orthopedic surgery.
- Control of pain and inflammation may vary from dog to dog.
- If PREVICOX Chewable Tablets are not given according to your veterinarian's directions, your dog's pain may return.
- Consult your veterinarian if your dog appears to be uncomfortable.

Which dogs should not take PREVICOX?

Your dog should not be given PREVICOX if he/she:

- Has an allergic reaction to firocoxib, the active ingredient in PREVICOX.
- Has had an allergic reaction (such as hives, facial swelling, or red or itchy skin) to aspirin or other NSAIDs.
- Is presently taking aspirin, other NSAIDs, or corticosteroids.
- Is under 12.5 pounds in body weight.
- Has pre-existing kidney or liver disease.
- Has decreased appetite, vomiting or diarrhea.

PREVICOX should only be given to dogs.

People should not take PREVICOX. Keep PREVICOX and all medications out of the reach of children. Call your physician immediately if you accidentally take PREVICOX.

What to tell/ask your veterinarian before giving PREVICOX.

Talk to your veterinarian about:

- The signs of osteoarthritis you have observed in your dog, such as limping or stiffness.
- The importance of weight control in the management of osteoarthritis.
- What tests might be done before PREVICOX is prescribed.
- How often your dog may need to be examined by your veterinarian.
- The risks and benefits of using PREVICOX. Serious adverse reactions, including death, have been associated with PREVICOX administration at doses above the recommended dose in puppies less than seven months of age.

Tell your veterinarian if your dog is currently experiencing or has ever had the following medical problems:

- Any side effects from taking PREVICOX or other NSAIDs, such as aspirin.
- Any digestive upset (vomiting and/or diarrhea).
- Any kidney disease.
- Any liver disease.

Tell your veterinarian about:

- Any other medical problems or allergies that your dog has now, or has had in the past.
- All medicines that you are giving or plan to give to your dog, including those you can get without a prescription and any dietary supplements.

Tell your veterinarian if your dog:

- Is under 7 months of age.
- Is pregnant, nursing or if you plan to breed your dog.

How to give PREVICOX to your dog.

PREVICOX should be given according to your veterinarian's instructions. Do not change the way you give PREVICOX to your dog without first speaking with your veterinarian. Your veterinarian will tell you what amount of PREVICOX is right for your dog and for how long it should be given. Most dogs will take PREVICOX Chewable Tablets from your hand, or you can place the tablet in your dog's mouth. PREVICOX may be given with or without food.

What are the possible side effects that may occur in my dog during PREVICOX therapy?

PREVICOX, like other NSAIDS, may cause some side effects. Serious side effects associated with NSAID therapy in dogs can occur with or without warning, and, in rare situations, result in death. The most common side effects associated with PREVICOX therapy involve the digestive tract (vomiting and decreased food consumption). Liver and kidney problems have also been reported with NSAIDs. Look for the following side effects that may indicate your dog is having a problem with PREVICOX:

- Decrease or increase in appetite.
- Vomiting.
- Change in bowel movements (such as diarrhea, or black, tarry or bloody stools).
- Change in behavior (such as decreased or increased activity level, incoordination, seizure, or aggression).
- Yellowing of gums, skin, or whites of the eyes (jaundice).
- Change in drinking habits (frequency or amount consumed).
- Change in urination habits (frequency, color, or smell).
- Change in skin (redness, scabs, or scratching).
- Unexpected weight loss.

It is important to stop the medication and contact your veterinarian immediately if you think your dog has a medical problem or side effect while taking PREVICOX tablets. If you have additional questions about possible side effects, talk with your veterinarian or call 1-888-637-4251.

Can PREVICOX be given with other medications?

PREVICOX should not be given with other NSAIDs (for example, aspirin, carprofen, etodolac, deracoxib, meloxicam, or tepoxalin) or corticosteroids (for example, prednisone, cortisone, dexamethasone, or triamcinolone).

Tell your veterinarian about all medications that you have given your dog in the past, and any medications you are planning to give with PREVICOX tablets. This should include other medicines that you can get without a prescription or any dietary supplements. Your veterinarian may want to check that all of your dog's medicines can be given together.

What do I do in case my dog eats more than the prescribed amount of PREVICOX?

Consult your veterinarian immediately if your dog eats more than the prescribed amount of PREVICOX.

What else should I know about PREVICOX?

- This sheet provides a summary of information about PREVICOX tablets. If you have any questions or concerns about PREVICOX, osteoarthritis pain, or postoperative pain following soft-tissue and orthopedic surgery, talk with your veterinarian.
- As with all prescribed medicines, PREVICOX tablets should only be given to the dog for which they were prescribed. They should be given to your dog only for the condition for which they were prescribed, at the prescribed dose.
- It is important to periodically discuss your dog's response to PREVICOX tablets. Your veterinarian will determine if your dog is responding as expected and if your dog should continue receiving PREVICOX tablets.

For technical assistance or to report suspected adverse reactions, call 1-888-637-4251.

For additional information about adverse drug experience reporting for animal drugs, contact FDA at 1-888-FDA-VETS or www.fda.gov/reportanimalae.

Approved by FDA under NADA # 141-230
©2019 Boehringer Ingelheim Animal Health USA Inc. All Rights Reserved.
®PREVICOX is a registered trademark of Boehringer Ingelheim Animal Health USA Inc.

Rev. 12-2018

BOEHRINGER INGELHEIM